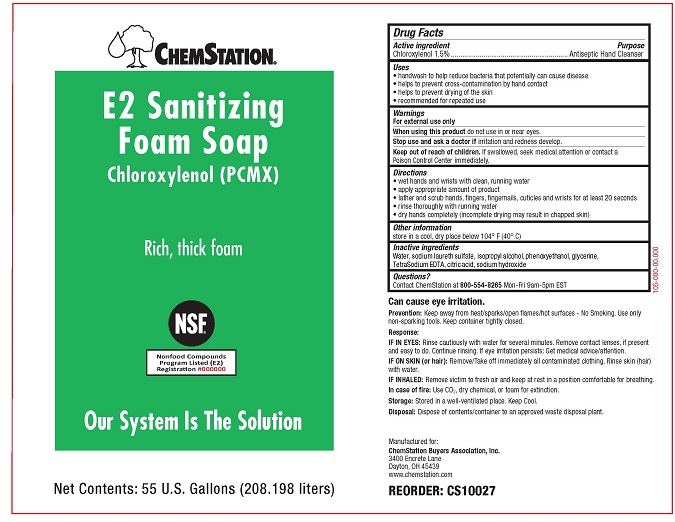 DRUG LABEL: Chemstation E2
NDC: 71212-103 | Form: SOAP
Manufacturer: Chemstation
Category: otc | Type: HUMAN OTC DRUG LABEL
Date: 20250109

ACTIVE INGREDIENTS: CHLOROXYLENOL 15 g/1 L
INACTIVE INGREDIENTS: WATER; ISOPROPYL ALCOHOL; EDETATE SODIUM; SODIUM HYDROXIDE; SODIUM LAURETH SULFATE; CITRIC ACID MONOHYDRATE; PHENOXYETHANOL; GLYCERIN

ChemStation E2 Sanitizing Foam Soap

Drug Facts

Active Ingredient

Chloroxylenol 1.5% w/w

Purpose

Antiseptic Hand Cleanser

Uses

- handwash to help reduce bacteria that potentially can cause disease
- helps to prevent cross contamination by hand contact
- helps to prevent drying of the skin
- recommended for repeated use

Warnings

For external use only

WHEN USING

When using this productdo not use in or near the eyes.

Stop use and ask a doctor ifirritation and redness develop.

Keep out of reach of children.If swallowed, seek medical attention or contact a Poison Control Center immediately.

Directions

- wet hands and wrists with clean, running water
- apply appropriate amount of product
- lather and scrub hands, fingers, fingernails, cuticles and wrists for at least 20 seconds
- rinse thoroughly with running water
- dry hands completely (incomplete drying may lead to chapped skin)

Other Information

store in a cool, dry place below 104° F (40° C)

Inactive Ingredients

Water, sodium laureth sulfate, isopropyl alcohol, phenoxyethanol, glycerine, TetraSodium EDTA, citric acid, sodium hydroxide

Questions?

Contact ChemStation at 800-554-8625Mon-Fri 9am - 5pm EST

OTHER SAFETY INFORMATION

Can cause eye irritation.

Prevention:Keep away from heat/sparks/open flames/hot surfaces - No Smoking. Use only non-sparking tools. Keep container tightly closed.

Response:

IF IN EYES:Rinse cautiously with water for several minutes. Remove contact lenses, if present and easy to do. Continue rinsing. If eye irritation persists: Get medical advice/attention.

IF ON SKIN (or hair):Remove/Take off immediately all contaminated clothing. Rinse skin (hair) with water.

IF INHALED:Remove victim to fresh air and keep at rest in a position comfortable for breathing.

In case of fire:Use CO2dry chemical, or foam for extinction.

Storage:Stored in a well-ventilated place. Keep Cool.

Disposal:Dispose of contents/container to an approved waste disposal plant.

Manufactured for:

ChemStation Buyers Association, Inc.

3400 Encrete Lane

Dayton, OH 45439

www.chemstation.com

PACKAGE LABEL

CHEMSTATION®

E2 Sanitizing Foam Soap

Chloroxylenol (PCMX)

Rich, thick foam

Our System Is The Solution

Net Contents: 55 U.S. Gallons (208.198 liters)